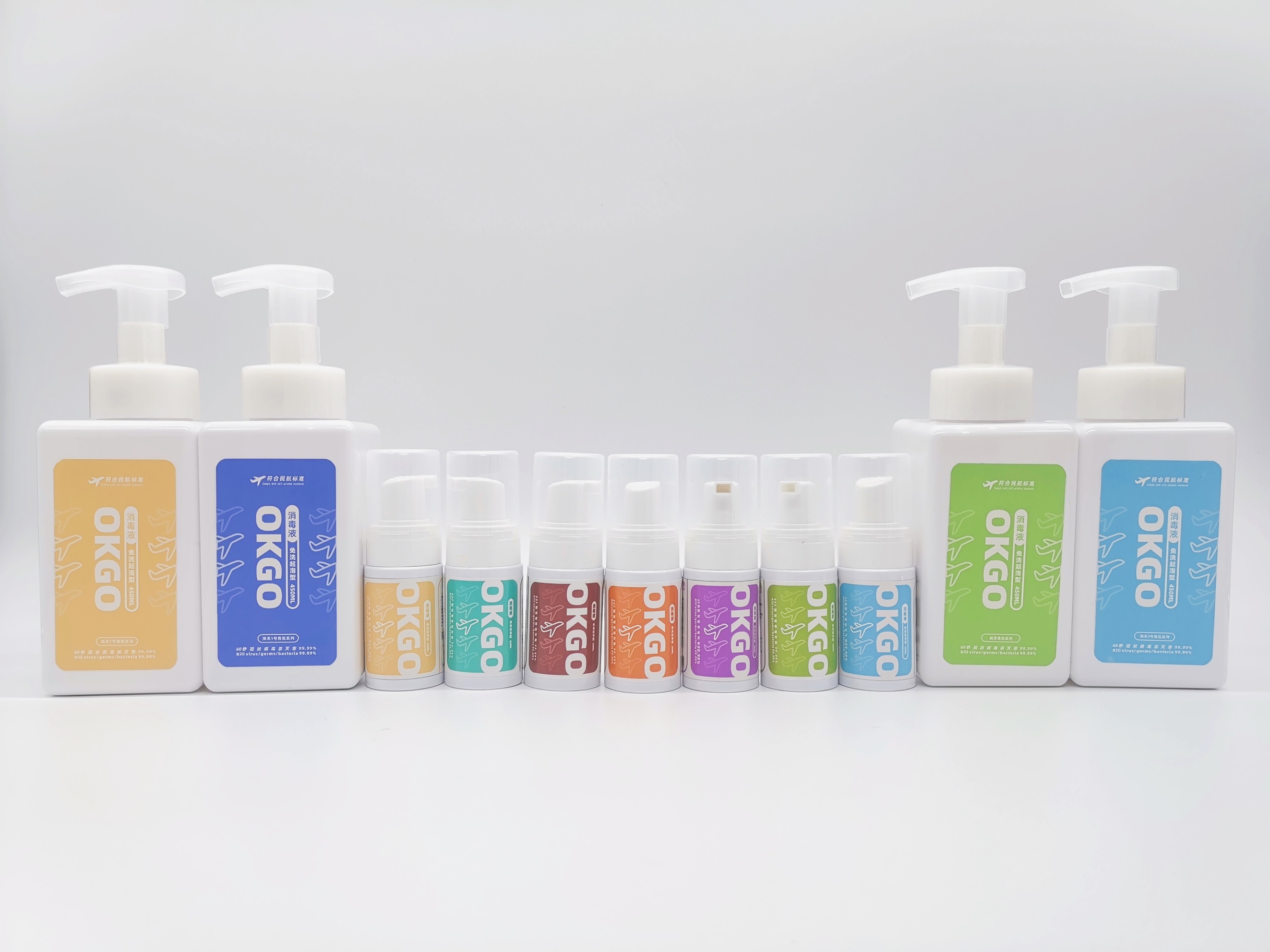 DRUG LABEL: OKGO Disinfectant
NDC: 81476-101 | Form: SPRAY
Manufacturer: Henan Seagood Medical Equipment Co., Ltd.
Category: otc | Type: HUMAN OTC DRUG LABEL
Date: 20210125

ACTIVE INGREDIENTS: DIDECYLDIMONIUM CHLORIDE 0.5 mg/1 mL
INACTIVE INGREDIENTS: BENZALKONIUM; (C10-C16)ALKYLDIMETHYLAMINE OXIDE; POLYETHYLENE GLYCOL, UNSPECIFIED; DIOCTYLDIMONIUM CHLORIDE; WATER; METHYL BENZOATE; TROLAMINE; STEARALKONIUM CHLORIDE

OKGO®Disinfectant

OKGO®Disinfectant

Active Ingredient(s)

Didecyl dimethyl ammonium chloride 0.5g/L. Purpose: Antiseptic

Purpose

Antiseptic

Use

OKGO®Disinfectant to help reduce bacteria that potentially can cause disease.

Warnings

For external use only.

Do not use

- in children less than 2 months of age
- on open skin wounds

When using this product keep out of eyes, ears, and mouth. In case of contact with eyes, rinse eyes thoroughly with water.
Stop use and ask a doctor if irritation or rash occurs. These may be signs of a serious condition.
Keep out of reach of children. If swallowed, get medical help or contact a Poison Control Center right away.

Stop use and ask a doctor if irritation or rash occurs. These may be signs of a serious condition.

Keep out of reach of children. If swallowed, get medical help or contact a Poison Control Center right away.

Directions

- Spray on the surface of human skin and let it dry naturally.
- Supervise children under 6 years of age when using this product to avoid swallowing.

Other information

- Store between 15-30C (59-86F)
- Avoid freezing and excessive heat above 40C (104F)

Inactive ingredients

Fatty alcohol polyoxyethylene ether
Dimethyldioctylammonium chloride
Dodecyldimethylbenzylammonium chloride
Benzyldimethylhexadecylammonium chloride
essence
water
Alkyl indican
triethanolamine